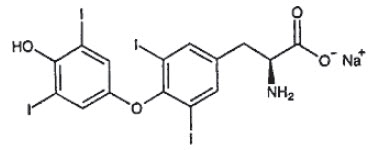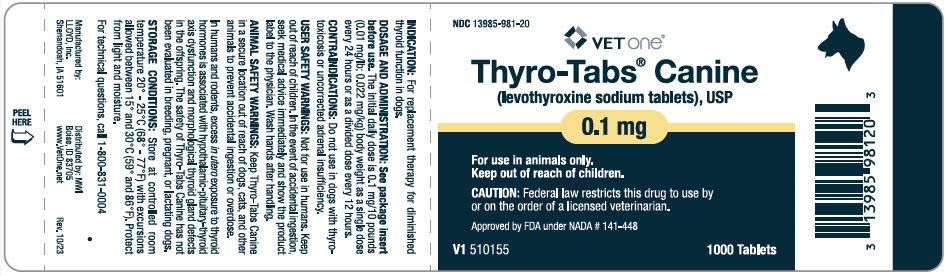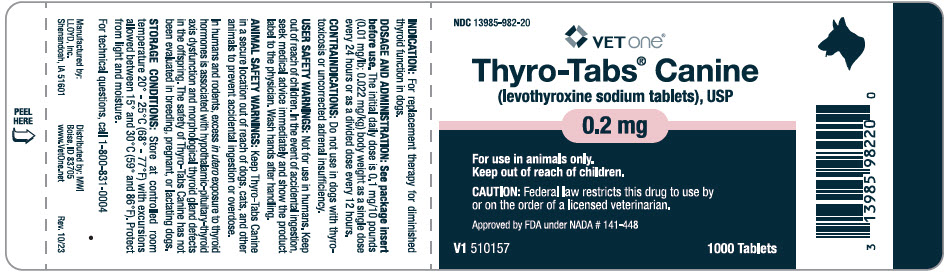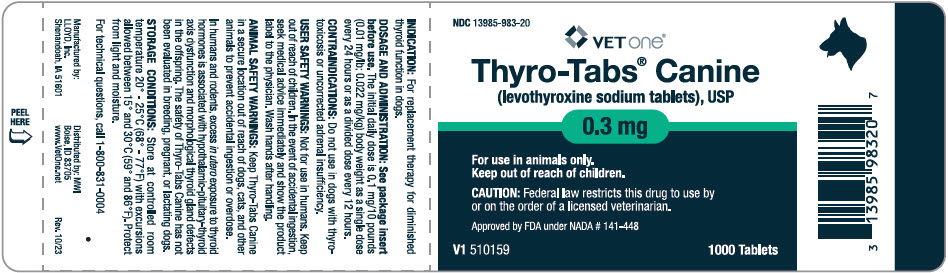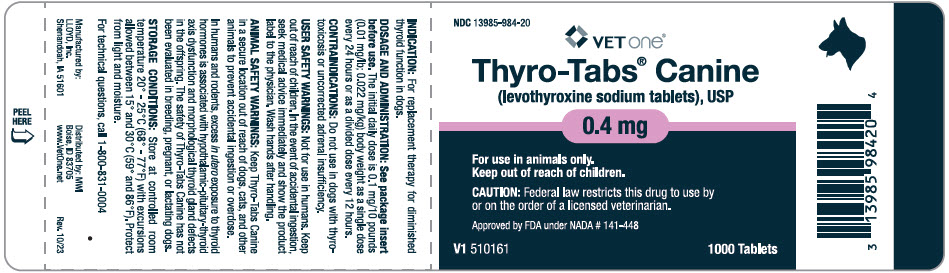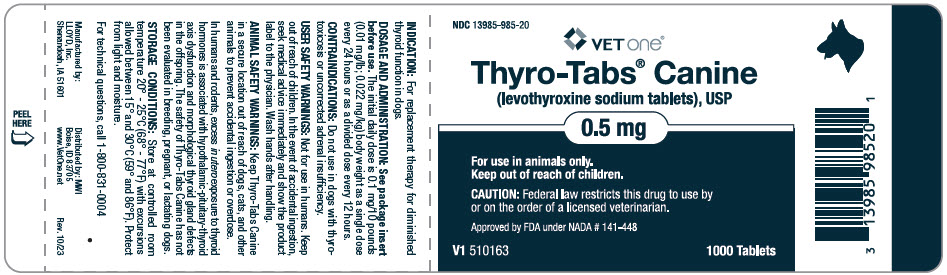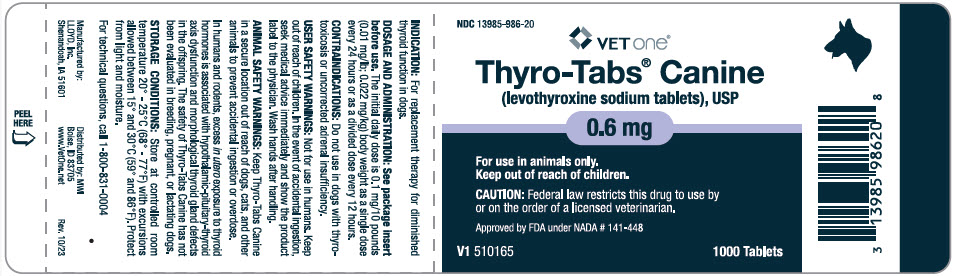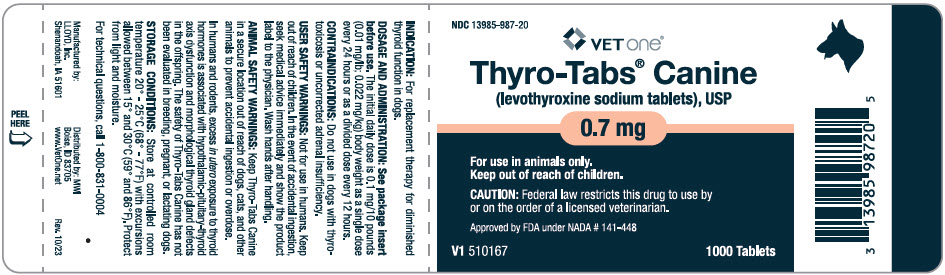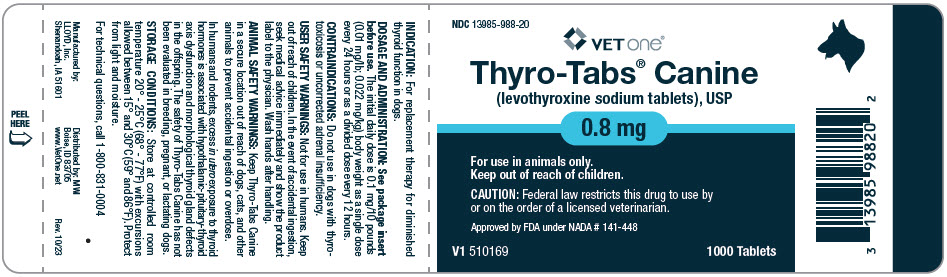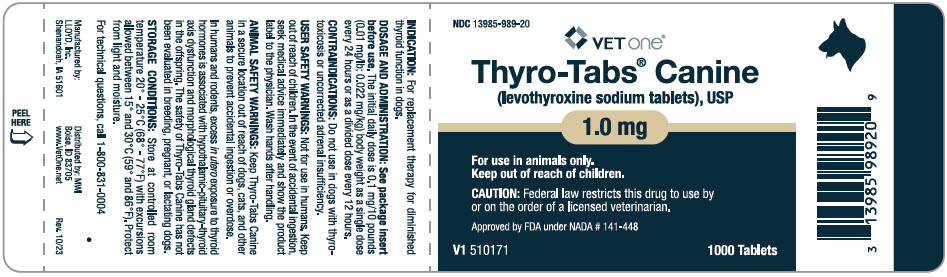 DRUG LABEL: Thyro-Tabs Canine
NDC: 13985-981 | Form: TABLET
Manufacturer: MWI/VetOne
Category: animal | Type: PRESCRIPTION ANIMAL DRUG LABEL
Date: 20241017

ACTIVE INGREDIENTS: LEVOTHYROXINE SODIUM 0.1 mg/1 1

Thyro-Tabs® Canine
(levothyroxine sodium tablets), USP

Synthetic thyroxine hormone

For oral use in dogs only.

WARNINGS

CAUTION: Federal (USA) law restricts this drug to use by or on the order of a licensed veterinarian.

DESCRIPTION

DESCRIPTION: Thyro-Tabs® Canine (levothyroxine sodium tablets), USP contains synthetic crystalline L-3,3' ,5,5'-tetraiodothyronine sodium salt [levothyroxine (T4) sodium]. Synthetic T4 is identical to that produced in the canine thyroid gland. Levothyroxine sodium has an empirical formula of C15H10I4N NaO4 ∙ H2O, molecular weight of 798.85 g/mol (anhydrous), and structural formula as shown:

VETERINARY INDICATIONS

INDICATION: For replacement therapy for diminished thyroid function in dogs.

DOSAGE AND ADMINISTRATION: The initial total daily dose is 0.1 mg/10 pounds (0.01 mg/lb; 0.022 mg/kg) body weight as a single dose every 24 hours or as a divided dose every 12 hours.

The dose may then be adjusted by monitoring the serum total thyroxine (TT4) concentrations 4 to 6 hours post-tablet administration, along with clinical response, of the dog every 4 to 8 weeks until an adequate maintenance dose is established.

To minimize day-to-day variations in serum TT4 concentrations (see CLINICAL PHARMACOLOGY), owners should consistently administer Thyro-Tabs Canine either with or without food.

When switching from another levothyroxine sodium formulation to Thyro-Tabs Canine, monitor serum TT4 concentrations and clinical response due to potential differences in recommended starting doses and potential differences in bioavailability.

CONTRAINDICATIONS

CONTRAINDICATIONS: Do not use in dogs with thyrotoxicosis or uncorrected adrenal insufficiency.

WARNINGS:

USER SAFETY WARNINGS: Not for use in humans. Keep out of reach of children. In the event of accidental ingestion, seek medical advice immediately and show the product label to the physician. Wash hands after handling.

ANIMAL SAFETY WARNINGS: Keep Thyro-Tabs Canine in a secure location out of reach of dogs, cats, and other animals to prevent accidental ingestion or overdose.

In humans and rodents, excess in utero exposure to thyroid hormones is associated with hypothalamic-pituitary-thyroid axis dysfunction and morphological thyroid gland defects in the offspring. The safefy of Thyro-Tabs Canine has not been evaluated In breeding, pregnant, or lactating dogs.

PRECAUTIONS

PRECAUTIONS: Dogs with underlying cardiac disease that are diagnosed with hypothyroidism should be closely monitored during the dose establishment phase. Adjustment of cardiac medication or levothyroxine sodium dosage may be needed depending on clinical response.^1-4

ADVERSE REACTIONS:

PRE-APPROVAL EXPERIENCE: In a 6-month US field study with 92 dogs, the most commonly reported adverse reactions by percentage of dogs experiencing the reaction included: anorexia (17%), dermatitis (15%), vomiting (15%), otitis externa (14%), lethargy (14%), polydipsia (13%), diarrhea (11 %), leukocytosis (9%), pruritus (8%), tachypnea (8%), polyuria (5%), hyperactivity (4%), and seborrhea (1 %).

One dog was withdrawn from the study at the owner's request because of increased water consumption and urination, which was possibly related to levothyroxine sodium.

Hematocrit and red blood cell counts exceeded the upper limit of the reference range in seven dogs by the end of the study. Liver enzyme (ALP, ALT, or AST) elevations related to levothyroxine administration were reported in three dogs. In two of the dogs with elevated ALT and AST, the elevations resolved by Day 70 and Day 126, respectively.

POST-APPROVAL EXPERIENCE (2022): The following adverse events are based on post-approval adverse drug experience reporting forThyro-Tabs Canine. Not all adverse events are reported to FDA/CVM. It is not always possible to reliably estimate the adverse event frequency or establish a causal relationship to product exposure using these data.

The following adverse events reported in dogs, are listed in decreasing order of reporting frequency: Pruritus, high or low serum thyroxine (T4) concentrations, tachypnea, weight loss, lethargy, anorexia, vomiting, polydipsia, alopecia, dermatitis, hyperactivity, diarrhea, and polyuria.

Allergic-type hypersensitivity reactions (including pruritus, hives, facial swelling, and dermatitis) have also been reported.

CONTACT INFORMATION: To report suspected adverse drug experiences, contact LLOYD, Inc. at 1-800-831-0004 or www.lloydinc.com. For additional information about adverse drug experience reporting for animal drugs, contact FDA at 1-888 FDA-VETS or www.fda.gov/reportanimalae.

CLINICAL PHARMACOLOGY

CLINICAL PHARMACOLOGY: Levothyroxine sodium has poor oral bioavailability in dogs (10-20%) with peak serum TT4 concentrations wilhin 4 to 6 hours (fasted state). Administration of levothyroxine sodium with food reduces oral bioavailability.^5 In most dogs, the estimated half-life is approximately 10-14 hours. Levothyroxine sodium is excreted in the feces.

EFFECTIVENESS: In a US field study with 92 dogs, dogs were administered a starling daily dose of 0.1 mg/10 lb (0.022 mg/kg) body weight. The dose was administered either once every 24 hours or as 0.05 mg/10 lb (0.011 mg/kg) body weight every 12 hours. The dose could be increased or decreased (without a change in frequency) after 6, 10, and 18 weeks, based on clinical findings and serum thyroid hormone concentrations. The maJority of the dogs (80%) were dosed at 0.08-0.12 mg/10 lb (0.008-0.012 mg/lb; 0.018-0.026 mg/kg) by the end of the study, with the majority of dogs (69.7%) requiring one dose change.

The product was considered effective if the serum TT4, free thyroxine (fT4), and thyroid stimulating hormone (TSH) concentrations were all within the desired treatment ranges when collected 4 to 6 hours post-tablet administration after 182 ± 5 days of treatment (TT4: 15-94 nmol/L; fT4: 8-36 pmol/L; TSH: ≤ 37 mU/L). Of the 78 evaluable cases, 59 (75.6%) were considered treatment successes. There was no statistical difference in lhe success rate between the once daily or divided dose treatment groups.

Clinical signs of hypothyroidism (weight gain, lethargy, bradycardia, seborrhea, alopecia, hyperpigmentation, scaling, and hypercholesterolemia) generally improved by the end of the study (Day 182 ± 5). Respiratory rate, excluding panting dogs, increased during the study along with activity level.

TARGET ANIMAL SAFETY: In a laboratory study, levothyroxine sodium was administered to 32 healthy, 7-10 month old, euthyroid Beagle dogs (4 males and 4 females per group) at 0×, 2×, 6×, and 10× the initial dose of 0.10 mg/10 lb (0.01 mg/lb) once daily for 26 weeks. Increased serum TT4 and fT4 concentrations were directly proportional to an increasing dose of levothyroxine sodium. Decreased serum TSH concentrations were inversely proportional to an increasing dose of levothyroxine sodium. Dogs treated with levothyroxine sodium had elevated red blood cell indices (hemoglobin, hematocrit, and red blood cell count) and ALT but these did not exceed the normal reference ranges. Dogs treated with levothyroxine sodium had lower albumin, calcium, globulins, and total protein values but these did not fall below the normal reference ranges. Vomiting, diarrhea, excitation, rapid respiration, tachycardia, and feces with blood were observed in all treatment groups, but were seen with greater frequency in dogs treated with levothyroxine sodium. Decreased pituitary gland and thyroid/parathyroid gland organ weights were also observed in euthyroid dogs treated with levothyroxine sodium.

STORAGE AND HANDLING

STORAGE CONDITIONS: Store at controlled room temperature 20°-25°C (68°-77°F) with excursions allowed between 15° and 30'C (59° and 86°F). Protect from light and moisture.

HOW SUPPLIED

HOW SUPPLIED: Thyro-Tabs Canine (levothyroxine sodium tablets), USP is available as scored, color coded ovoid tablets in 9 strengths: 0.1 mg-yellow; 0.2 mg-pink; 0.3 mg-green; 0.4 mg-maroon; 0.5 mg-white; 0.6 mg-purple; 0.7 mg-orange; 0.8 mg-blue; and 1.0 mg-tan, in bottles of 120 and 1,000 tablets.

Approved by FDA under NADA # 141-448

Manufactured by:
LLOYD, Inc.
Shenandoah, IA 51601

Distributed by: MWI
Boise, ID 83705
www.VetOne.net

VET one®

Rev. 10/23

REFERENCES:

1. Phillips DE, Harkin KR. Hypothyroidism and myocardial failure in two Great Danes. J Am Anim Hosp Assoc 2003;39:133-137.
2. Flood JA, Hoover JP. Improvement in myocardial dysfunction in a hypothyroid dog. Can Vet J 2009;50:828-834.
3. Chow B, French A. Conversion of atrial fibrillation after levothyroxine in a dog with hypothyroidism and arterial thromboembolism. J Small Anim Pract 2014;55:278-282.
4. Sangster JK, Panciera DL, Abbott JA. Cardiovascular effects of thyroid disease. Compend Contin Educ Vet 2013;35:E5.
5. Le Traon G, Burgaud S, Horspool LJ. Pharmacokinetics of total thyroxine in dogs after administration of an oral solution of levothyroxine sodium. J Vet Pharmacol Ther 2008;31:95-101.

For technical questions, call 1-800-831-0004

PRINCIPAL DISPLAY PANEL - 0.1 mg Tablet Bottle Label

NDC 13985-981-20

VET one®

Thyro-Tabs® Canine
(levothyroxine sodium tablets), USP

0.1 mg

For use in animals only.
Keep out of reach of children.

CAUTION: Federal law restricts this drug to use by
or on the order of a licensed veterinarian.

Approved by FDA under NADA # 141-448

V1 510155
1000 Tablets

PRINCIPAL DISPLAY PANEL - 0.2 mg Tablet Bottle Label

NDC 13985-982-20

VET one®

Thyro-Tabs® Canine
(levothyroxine sodium tablets), USP

0.2 mg

For use in animals only.
Keep out of reach of children.

CAUTION: Federal law restricts this drug to use by
or on the order of a licensed veterinarian.

Approved by FDA under NADA # 141-448

V1 510157
1000 Tablets

PRINCIPAL DISPLAY PANEL - 0.3 mg Tablet Bottle Label

NDC 13985-983-20

VET one®

Thyro-Tabs® Canine
(levothyroxine sodium tablets), USP

0.3 mg

For use in animals only.
Keep out of reach of children.

CAUTION: Federal law restricts this drug to use by
or on the order of a licensed veterinarian.

Approved by FDA under NADA # 141-448

V1 510159
1000 Tablets

PRINCIPAL DISPLAY PANEL - 0.4 mg Tablet Bottle Label

NDC 13985-984-20

VET one®

Thyro-Tabs® Canine
(levothyroxine sodium tablets), USP

0.4 mg

For use in animals only.
Keep out of reach of children.

CAUTION: Federal law restricts this drug to use by
or on the order of a licensed veterinarian.

Approved by FDA under NADA # 141-448

V1 510161
1000 Tablets

PRINCIPAL DISPLAY PANEL - 0.5 mg Tablet Bottle Label

NDC 13985-985-20

VET one®

Thyro-Tabs® Canine
(levothyroxine sodium tablets), USP

0.5 mg

For use in animals only.
Keep out of reach of children.

CAUTION: Federal law restricts this drug to use by
or on the order of a licensed veterinarian.

Approved by FDA under NADA # 141-448

V1 510163
1000 Tablets

PRINCIPAL DISPLAY PANEL - 0.6 mg Tablet Bottle Label

NDC 13985-986-20

VET one®

Thyro-Tabs® Canine
(levothyroxine sodium tablets), USP

0.6 mg

For use in animals only.
Keep out of reach of children.

CAUTION: Federal law restricts this drug to use by
or on the order of a licensed veterinarian.

Approved by FDA under NADA # 141-448

V1 510165
1000 Tablets

PRINCIPAL DISPLAY PANEL - 0.7 mg Tablet Bottle Label

NDC 13985-987-20

VET one®

Thyro-Tabs® Canine
(levothyroxine sodium tablets), USP

0.7 mg

For use in animals only.
Keep out of reach of children.

CAUTION: Federal law restricts this drug to use by
or on the order of a licensed veterinarian.

Approved by FDA under NADA # 141-448

V1 510167
1000 Tablets

PRINCIPAL DISPLAY PANEL - 0.8 mg Tablet Bottle Label

NDC 13985-988-20

VET one®

Thyro-Tabs® Canine
(levothyroxine sodium tablets), USP

0.8 mg

For use in animals only.
Keep out of reach of children.

CAUTION: Federal law restricts this drug to use by
or on the order of a licensed veterinarian.

Approved by FDA under NADA # 141-448

V1 510169
1000 Tablets

PRINCIPAL DISPLAY PANEL - 1.0 mg Tablet Bottle Label

NDC 13985-989-20

VET one®

Thyro-Tabs® Canine
(levothyroxine sodium tablets), USP

1.0 mg

For use in animals only.
Keep out of reach of children.

CAUTION: Federal law restricts this drug to use by
or on the order of a licensed veterinarian.

Approved by FDA under NADA # 141-448

V1 510171
1000 Tablets